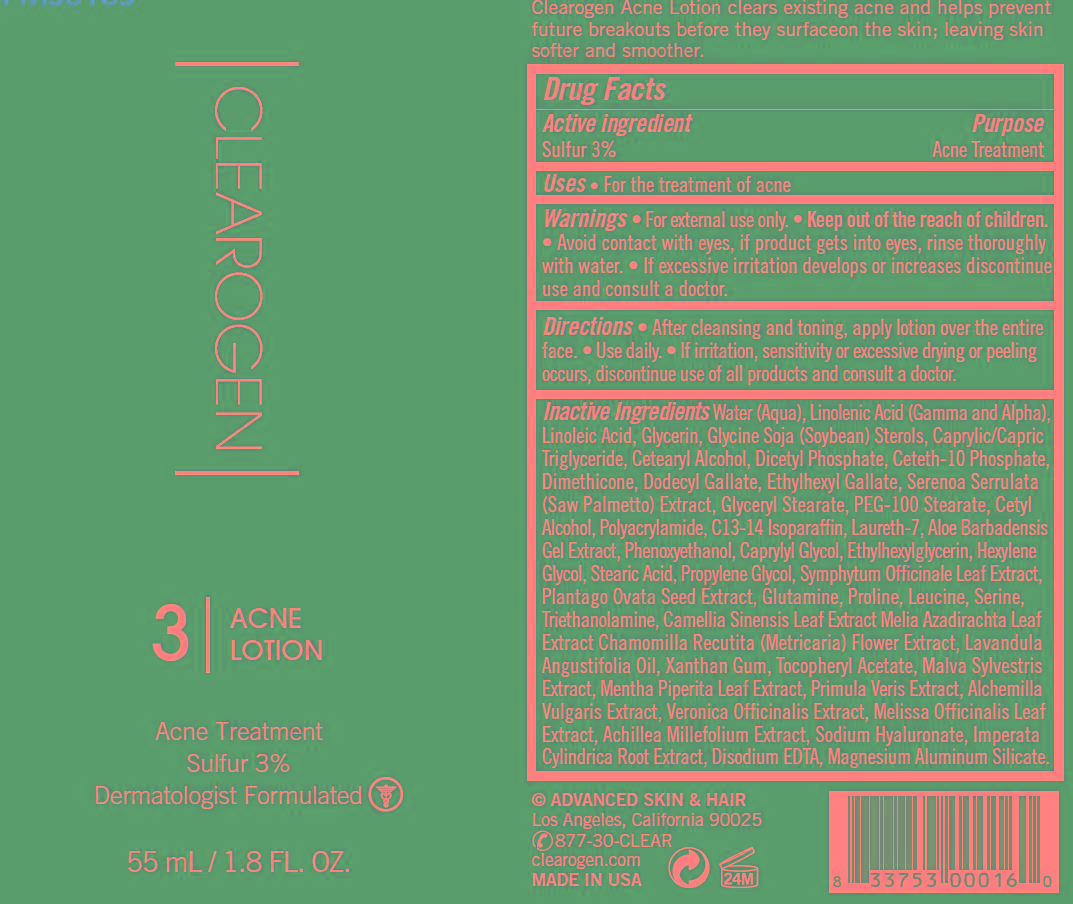 DRUG LABEL: Acne LotionSulfur
          
NDC: 62742-4169 | Form: LOTION
Manufacturer: Allure Labs Inc
Category: otc | Type: HUMAN OTC DRUG LABEL
Date: 20181109

ACTIVE INGREDIENTS: Sulfur 30 mg/1 mL
INACTIVE INGREDIENTS: WATER; LINOLENIC ACID; LINOLEIC ACID; GLYCERIN; SOYBEAN; PEG-6 CAPRYLIC/CAPRIC GLYCERIDES; CETOSTEARYL ALCOHOL; DIHEXADECYL PHOSPHATE; CETETH-10 PHOSPHATE; DIMETHICONE; DODECYL GALLATE; ETHYLHEXYL GALLATE; SAW PALMETTO; GLYCERYL MONOSTEARATE; PEG-100 STEARATE; CETYL ALCOHOL; POLYACRYLAMIDE (1500 MW); C13-14 ISOPARAFFIN ; LAURETH-7; ALOE VERA LEAF; PHENOXYETHANOL  ; CAPRYLYL GLYCOL; ETHYLHEXYLGLYCERIN  ; HEXYLENE GLYCOL; STEARIC ACID; PROPYLENE GLYCOL; COMFREY LEAF; PLANTAGO OVATA SEED; GLUTAMINE; PROLINE; LEUCINE; SERINE; TROLAMINE ; GREEN TEA LEAF; AZADIRACHTA INDICA LEAF; CHAMOMILE; LAVENDER OIL; XANTHAN GUM; .ALPHA.-TOCOPHEROL ACETATE; MENTHA PIPERITA LEAF; PRIMULA VERIS ; ALCHEMILLA XANTHOCHLORA FLOWERING TOP; MELISSA OFFICINALIS LEAF; ACHILLEA MILLEFOLIUM ; HYALURONATE SODIUM; IMPERATA CYLINDRICA ROOT; EDETATE DISODIUM; MAGNESIUM ALUMINUM SILICATE

DRUG FACTS

Active Ingredients: Sulfur 3%

Purpose: Acne Treatment

INDICATIONS AND USAGE

Uses: For the treatment of acne

Warning:

- For external use only
- Avoid contact with eyes, if product get into eyes, rinse thoroughly with water.
- If excessive irritation develops or increases discontinue use and consult a doctor.

Keep Out of the reach of children.

Directions:

- After cleansing and toning apply lotion over the entire face.
- Use daily.
- If going outside use a sunscreen.
- Allow Clearogen to dry then follow directions in the sunscreen labeling.
- If irritation or sensitivity develops, discontinue use of all products and consult a doctor.

INACTIVE INGREDIENT

Aqua, Lenolenic Acid, Lenoleic Acid, Glycerine, Soybeen, PEG-6 Caprylic/Capric glycerides, Cetostearyl acohol, Dihexadecyl phosphate, Ceteth-10 phosphate, Dimethicone, Dodecyl gallate, Ethylhexyl gallate, Saw palmetto, Glyceryl monostearate, PEG-100 stearate, Cetyl alcohol, Polyacrylamide, C13- 14 Isoparaffin, Laureth-7, Aloe vera leaf, Phenoxyethanol, Calrylyl Glycol, Ethylhexyl glycerin, Hexylene glycol, Stearic acid, Propylene glycol, Comfrey leaf, Plantago ovata seed, Glutamine, Proline, Leucine, Serine, Trolamine, Green tea leaf, Azadirachta indica leaf, Chamomile, Levender oil, Xantham gum, Alpha-tocopherol acetate, Malva sylvestris extract, Melissa officinalis leaf, Achillea Millefolium, Sodium hyaluronate, Imperata Cylendrica root, Edetate disodium, Magnesium aluminum silicate.

PACKAGE LABEL

Advanced Skin & Hair

Los Angeles, California 90025

877-30-CLEAR

clearogen.com

Made In USA